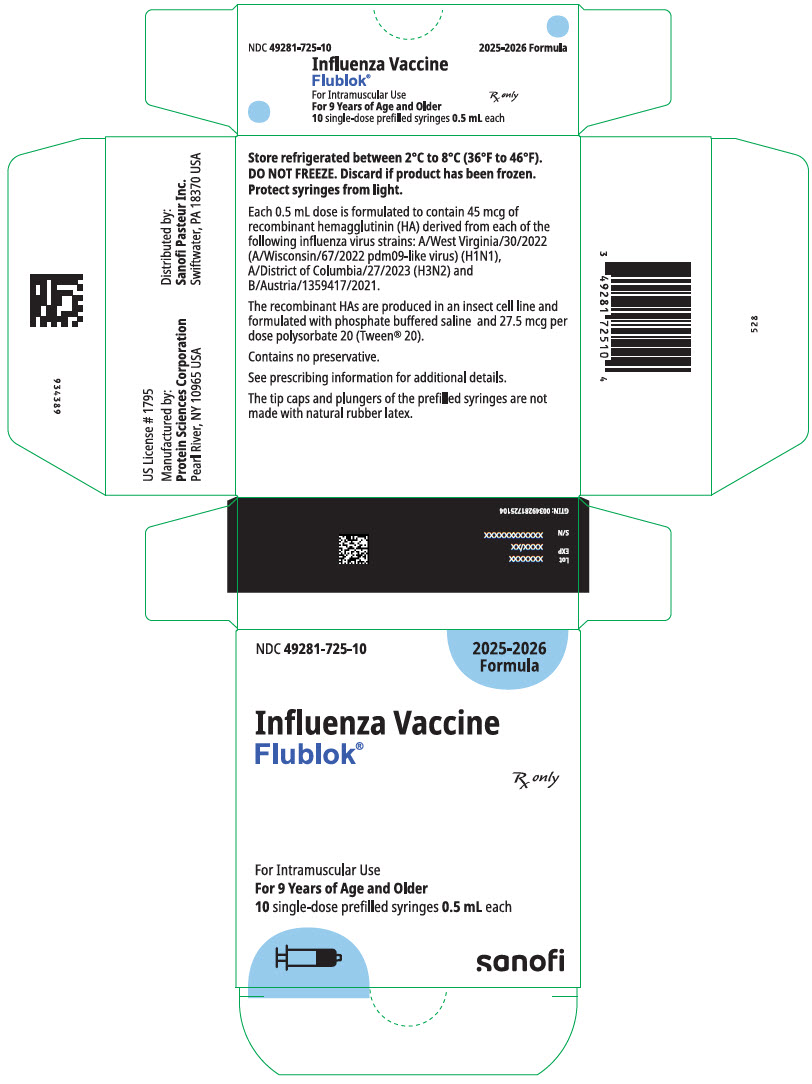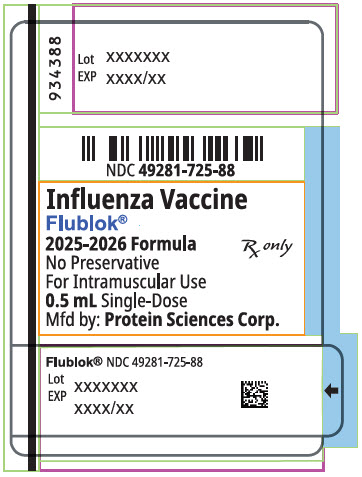 DRUG LABEL: FLUBLOK TRIVALENT NORTHERN HEMISPHERE
NDC: 49281-725 | Form: INJECTION
Manufacturer: Sanofi Pasteur Inc.
Category: other | Type: VACCINE LABEL
Date: 20250702

ACTIVE INGREDIENTS: INFLUENZA A VIRUS A/WEST VIRGINIA/30/2022 (H1N1) RECOMBINANT HEMAGGLUTININ ANTIGEN 45 ug/0.5 mL; INFLUENZA A VIRUS A/DISTRICT OF COLUMBIA/27/2023 (H3N2) RECOMBINANT HEMAGGLUTININ ANTIGEN 45 ug/0.5 mL; INFLUENZA B VIRUS B/AUSTRIA/1359417/2021 RECOMBINANT HEMAGGLUTININ ANTIGEN 45 ug/0.5 mL
INACTIVE INGREDIENTS: SODIUM PHOSPHATE, MONOBASIC, MONOHYDRATE; SODIUM PHOSPHATE, DIBASIC, DODECAHYDRATE; SODIUM CHLORIDE; POLYSORBATE 20; OCTOXYNOL-9; WATER

HIGHLIGHTS OF PRESCRIBING INFORMATION

These highlights do not include all the information needed to use Flublok® safely and effectively. See full prescribing information for Flublok.
Flublok (Influenza Vaccine) injection, for intramuscular use
2025-2026 Formula
Initial U.S. Approval: 2013

RECENT MAJOR CHANGES

Indications and Usage (1) | 03/2025

1 INDICATIONS AND USAGE

Flublok is a vaccine indicated for active immunization for the prevention of disease caused by influenza A virus subtypes and influenza type B virus represented by antigens contained in the vaccine. Flublok is approved for use in individuals 9 years of age and older. (1)

2 DOSAGE AND ADMINISTRATION

For intramuscular use (0.5 mL). (2)

3 DOSAGE FORMS AND STRENGTHS

Flublok is an injection, a single dose is 0.5mL. (3)

4 CONTRAINDICATIONS

Do not administer Flublok to anyone with a history of severe allergic reactions (e.g., anaphylaxis) to any component of the vaccine. (4, 6.2, 11)

5 WARNINGS AND PRECAUTIONS

- Appropriate medical treatment must be immediately available to manage potential anaphylactic reactions following administration of Flublok. (5.1)
- If Guillain-Barré syndrome has occurred within 6 weeks of receipt of a prior influenza vaccine, the decision to give Flublok should be based on careful consideration of potential benefits and risks. (5.2)

6 ADVERSE REACTIONS

- In children 9 through 17 years of age who received Flublok Quadrivalent, the most common (≥10%) solicited injection-site adverse reaction was pain (34.4%). The most common (≥10%) solicited systemic adverse reaction was myalgia (19.3%), headache (18.5%) and malaise (16.1%). (6.1)
- In adults 18 through 49 years of age who received Flublok, the most common (≥10%) injection-site adverse reaction was pain (37%); the most common (≥10%) solicited systemic adverse reactions were headache (15%), fatigue (15%) and muscle pain (11%). (6.1)
- In adults 50 through 64 years of age who received Flublok, the most common (≥10%) injection site adverse reaction was pain (32%); the most common (≥10%) solicited systemic adverse reactions were headache (17%), fatigue (13%), and muscle pain (11%). (6.1)
- In adults 65 years of age and older who received Flublok, the most common (≥10%) injection site adverse reaction was pain (19%); the most common (≥10%) solicited systemic adverse reactions were fatigue (13%) and headache (10%). (6.1)

To report SUSPECTED ADVERSE REACTIONS, contact Sanofi Pasteur Inc., at (1-800-822-2463 (1-800-Vaccine) or VAERS at 1-800-822-7967 or www.vaers.hhs.gov.

FULL PRESCRIBING INFORMATION

1 INDICATIONS AND USAGE

Flublok is a vaccine indicated for active immunization for the prevention of disease caused by influenza A virus subtypes and influenza type B virus represented by antigens contained in the vaccine. Flublok is approved for use in individuals 9 years of age and older.

2 DOSAGE AND ADMINISTRATION

For intramuscular use.

2.1 Dosage

Administer Flublok as a single 0.5 mL dose.

2.2 Administration

Parenteral drug products should be inspected visually for particulate matter and discoloration prior to administration whenever solution and container permit. If either of these conditions exists, the vaccine should not be administered.

Gently invert the prefilled syringe prior to affixing a sterile needle.

Administer the dose intramuscularly.

3 DOSAGE FORMS AND STRENGTHS

Flublok is an injection. A single dose is 0.5 mL.

4 CONTRAINDICATIONS

Do not administer Flublok to anyone with a history of severe allergic reactions (e.g., anaphylaxis) to any component of the vaccine. [see Postmarketing Experience [6.2] and Description (11)].

5 WARNINGS AND PRECAUTIONS

5.1 Managing Allergic Reactions

Appropriate medical treatment must be immediately available to manage potential anaphylactic reactions following administration of Flublok.

5.2 Guillain-Barré Syndrome

If GBS has occurred within 6 weeks of receipt of a prior influenza vaccine, the decision to give Flublok should be based on careful consideration of the potential benefits and risks.

The 1976 swine influenza vaccine was associated with an increased frequency of Guillain-Barré Syndrome (GBS). Evidence for a causal relation of GBS with other influenza vaccines is inconclusive; if an excess risk exists, it is probably slightly more than one additional case per 1 million persons vaccinated.

5.3 Altered Immunocompetence

If Flublok is administered to immunocompromised individuals, including persons receiving immunosuppressive therapy, the immune response may be diminished.

5.4 Limitations of Vaccine Effectiveness

Vaccination with Flublok may not protect all vaccine recipients.

5.5 Syncope

Syncope (fainting) has been reported following vaccination with Flublok. Procedures should be in place to avoid injury from fainting.

6 ADVERSE REACTIONS

In children and adolescents 9 through 17 years of age who received Flublok Quadrivalent, the most common (≥10%) solicited injection-site adverse reaction was pain (34.4%). The most common (≥10%) solicited systemic adverse reactions were myalgia (19.3%), headache (18.5%) and malaise (16.1%). (6.1).

In adults 18 through 49 years of age who received Flublok, the most common (≥10%) injection-site adverse reaction was pain (37%); the most common (≥10%) solicited systemic adverse reactions were headache (15%), fatigue (15%) and muscle pain (11%). (6.1)

In adults 50 through 64 years of age who received Flublok, the most common (≥10%) injection site adverse reaction was pain (32%); the most common (≥10%) solicited systemic adverse reactions were headache (17%), fatigue (13%), and muscle pain (11%). (6.1)

In adults 65 years of age and older who received Flublok, the most common (≥10%) injection site adverse reaction was pain (19%); the most common (≥10%) solicited systemic adverse reactions were fatigue (13%) and headache (10%). (6.1)

6.1 Clinical Trials Experience

Because clinical studies are conducted under widely varying conditions, adverse reaction rates observed in the clinical studies of a vaccine cannot be directly compared to rates in the clinical studies of another vaccine and may not reflect the rates observed in clinical practice.

The safety experience with Flublok Quadrivalent is relevant to Flublok because both vaccines are manufactured using the same process and have overlapping compositions.

Flublok

Flublok has been administered to and safety data collected from 2497 adults 18 through 49 years of age, 972 adults 50 through 64 years of age, and 1078 adults aged 65 years and older enrolled in five randomized, placebo- or active-controlled clinical trials. Clinical safety data for Flublok are presented from four clinical trials (Studies 1, 2, 3, and 4). Data from a placebo-controlled trial in adults 18 through 49 years of age (Study 1) are presented, followed by data pooled according to age group from Studies 2 and 4 (adults 50 through 64 years of age) and Studies 3 and 4 (adults aged 65 years and older).

Reactogenicity data from a small Phase 2 trial (Study 5) in adults 18 through 49 years of age, 153 of whom received Flublok 135mcg, are not presented. However, subjects from Study 5 are included in the description of deaths and serious adverse events (SAEs). In all studies local (injection site) and systemic adverse reactions were solicited with the use of a memory aid for 7 days following vaccination, and unsolicited adverse reactions were collected for 28-30 days post-vaccination. In Studies 1, 2, 3, and 5, SAEs were collected for 6 months post-vaccination via clinic visit or telephone follow up on Day 28, telephone follow up on Day 180, or by spontaneous reporting. Study 4 collected SAEs through 30 days following receipt of vaccine. Study 4 also actively solicited pre-specified common hypersensitivity-type reactions through 30 days following receipt of vaccine as a primary endpoint.

Study 1 (NCT00539981) included 4648 subjects 18 through 49 years of age for safety analysis, randomized to receive Flublok (n=2344) or placebo (n=2304) (see Clinical Studies [14.1]).

Study 2 (NCT00539864) included 602 subjects 50 through 64 years of age for safety analysis, randomized to receive Flublok (n=300) or another U.S.-licensed trivalent influenza vaccine (Fluzone, manufactured by Sanofi Pasteur, Inc.) as an active control (n=302).

Study 3 (NCT00395174) included 869 subjects aged 65 years and older for safety analysis, randomized to receive Flublok (n=436) or another U.S.-licensed trivalent influenza vaccine (Fluzone) as an active control (n=433).

Study 4 (NCT01825200) included 2627 subjects aged 50 years and older for safety analysis, randomized to receive Flublok (n=1314) or another U.S.-licensed trivalent influenza vaccine (Afluria, manufactured by bioCSL Pty Ltd.) as an active control (n=1313). Among subjects 50 through 64 years of age, 672 received Flublok and 665 received Afluria. Among subjects aged 65 years and older, 642 received Flublok and 648 received Afluria.

Study 5 (NCT00328107) included 307 subjects aged 18 through 49 years in the safety analysis population who received Flublok (n=153) or Placebo (n=154).

In a clinical trial of adults 18 through 49 years of age (Study 1,) the mean age of participants was 32.5 years, 59% were female, and 67% were Caucasian (see Clinical Studies [14.1]). Solicited local and systemic adverse reactions reported within 7 days after vaccination were self-reported in paper diaries or were reported by an investigator, and are presented in Table 1.

Table 1: Frequency of Solicited Local Injection Site Adverse Reactions and Systemic Adverse Reactions within 7 Days of Administration of Flublok or Placebo in Adults 18 through 49 Years of Age, Study 1, Total Vaccinated Cohort [Total Vaccinated Cohort is defined as all randomized subjects who received study vaccine according to the treatment actually received and who provided data.] , [Study 1 is registered as NCT00539981 under the National Clinical Trials registry.] , [Denominators for Study 1: The total number of enrolled, randomized, and vaccinated subjects was 2344 in the Flublok group and 2304 in the placebo group. For all categories except fever, the number of subjects with missing values was 72 in the Flublok group and 73 in the Placebo group so that these denominators are 2272 and 2231 respectively. For fever, 89 Flublok recipients and 104 Placebo recipients were missing data, making these denominators 2255 and 2200 respectively.]
 | Flublok N=2272 |  |  | Placebo N=2231
Local | % |  |  | %
 | Any | Mod [Moderate = had it, and it was bad enough to prevent a significant part of usual activities; Severe = had it, and it prevented most or all of normal activities, or had to see a doctor for prescription medicine.] | Sev | Any | Mod | Sev
Pain | 37 | 2 | <1 | 8 | <1 | <1
Redness | 4 | <1 | <1 | 2 | <1 | <1
Swelling | 3 | <1 | <1 | 2 | <1 | <1
Bruising | 3 | <1 | <1 | 3 | <1 | <1
Systemic | % |  |  | %
Headache | 15 | 3 | <1 | 16 | 3 | <1
Fatigue | 15 | 3 | <1 | 14 | 3 | <1
Muscle Pain | 11 | 2 | <1 | 7 | <1 | <1
Nausea | 6 | 1 | <1 | 5 | 1 | <1
Joint pain | 4 | <1 | <1 | 4 | <1 | <1
Chills | 3 | <1 | <1 | 3 | <1 | <1
Fever [Fever defined as ≥100.4°F (38°C). Mild (≥100.4° to <101.1°F); Moderate (≥101.2°F to <102.2°F); Severe (≥102.2°F)] | <1 | <1 | <1 | <1 | <1 | <1
NOTE: Data based on the most severe response reported by subjects. Results ≥1% reported to nearest whole percent; results >0 but <1% reported as <1%.

Across three clinical trials (Studies 2, 3 and 4, Tables 2 and 3) a total of 2050 adults ages 50 years and older received Flublok and 2048 received a U.S.-licensed trivalent inactivated influenza vaccine (IIV3) comparator. The mean age of Flublok study participants was 65 years; 56% were female and 80% were Caucasian.

The incidence of solicited reactogenicity differed between adults 50 through 64 years of age and adults aged 65 years and older. Therefore, data from Studies 2, 3, and 4 were pooled according to age group and are presented separately (Tables 2 and 3). Solicited local and systemic adverse reactions reported within 7 days after vaccination in adults 50 through 64 years of age were self-reported in paper diaries or were reported by an investigator, and are presented in Table 2.

Most adverse reactions in both age groups were mild in severity.

Table 2: Frequency of Solicited Local Injection Site Adverse Reactions and Systemic Adverse Reactions within 7 Days of Administration of Flublok or Comparator in Adults 50 through 64 Years of Age, Studies 2 and 4, Total Vaccinated Cohort [Total Vaccinated Cohort is defined as all randomized subjects who received study vaccine according to the treatment actually received and who provided data.] , [Pooled Data from Studies 2 and 4. For Studies 2 and 4, the U.S.-licensed IIV3 comparators were Fluzone and Afluria, respectively. Studies 2 and 4 are registered as NCT00539864 and NCT01825200, respectively, under the National Clinical Trials registry.]
 | Flublok N=972 |  |  | IIV3 N=967
 | Any | Mod [Moderate = had it, and it was bad enough to prevent a significant part of usual activities; Severe = had it, and it prevented most or all of normal activities, or had to see a doctor for prescription medicine.] | Sev | Any | Mod | Sev
Local | %
Pain | 32 | 2 | <1 | 37 | <1 | 0
Firmness/Swelling | 7 | 2 | <1 | 6 | 1 | <1
Redness | 6 | 2 | <1 | 5 | 1 | <1
Systemic | %
Headache | 17 | 4 | <1 | 16 | 3 | <1
Fatigue | 13 | 3 | <1 | 17 | 3 | <1
Muscle Pain | 11 | 2 | <1 | 11 | 2 | <1
Joint Pain | 8 | 2 | <1 | 8 | 2 | <1
Nausea | 6 | 1 | 0 | 5 | <1 | <1
Shivers/Chills | 5 | 1 | 0 | 4 | <1 | <1
Fever [Fever defined as ≥100.4°F (38°C). Mild (≥100.4° to <101.1°F); Moderate (≥101.2°F to <102.2°F); Severe (≥102.2°F) For fever, 12 Flublok recipients and 5 IIV3 recipients were missing data, making these denominators 964 and 962, respectively.] | <1 | <1 | <1 | <1 | 0 | 0
NOTE: Data based on the most severe response reported by subjects. Results ≥1% reported to nearest whole percent; results >0 but <1% reported as <1%.

Solicited local and systemic adverse reactions reported within 7 days after vaccination in adults ≥65 years of age were self-reported in paper diaries or were reported by an investigator, and are presented in Table 3.

Table 3: Frequency of Solicited Local Injection Site Adverse Reactions and Systemic Adverse Reactions within 7 Days of Administration of Flublok or Comparator in Adults ≥65 Years of Age, Studies 3 and 4, Total Vaccinated Cohort [Total Vaccinated Cohort is defined as all randomized subjects who received study vaccine according to the treatment actually received and who provided data.] , [Pooled Data from Studies 3 and 4. For Studies 3 and 4, the U.S.-licensed IIV3 comparators were Fluzone and Afluria, respectively. Studies 3 and 4 are registered as NCT00395174 and NCT01825200, respectively, under the National Clinical Trials registry.]
 | Flublok N=1078 |  |  | IIV3 N=1081
 | Any | Mod [Moderate = had it, and it was bad enough to prevent a significant part of usual activities; Severe = had it, and it prevented most or all of normal activities, or had to see a doctor for prescription medicine.] | Sev | Any | Mod | Sev
Local | %
Pain | 19 | <1 | <1 | 20 | <1 | <1
Redness | 7 | 1 | <1 | 7 | 1 | 1
Firmness/Swelling | 7 | 2 | <1 | 7 | <1 | <1
Systemic | %
Fatigue | 13 | 3 | <1 | 15 | 2 | <1
Headache | 10 | <1 | <1 | 9 | 1 | <1
Muscle Pain | 8 | 2 | <1 | 8 | 1 | <1
Joint Pain | 6 | 1 | <1 | 6 | 1 | <1
Shivers/Chills | 5 | <1 | <1 | 5 | <1 | <1
Nausea | 4 | <1 | <1 | 3 | <1 | <1
Fever [Fever defined as ≥100.4°F (38°C). Mild (≥100.4° to <101.1°F); Moderate (≥101.2°F to <102.2°F); Severe (≥102.2°F)] | 3 | <1 | <1 | 2 | 0 | 0
NOTE: Data based on the most severe response reported by subjects. Results ≥1% reported to nearest whole percent; results >0 but <1% reported as <1%.

Among adults 18 through 49 years of age (Studies 1 and 5 pooled), through 6 months post-vaccination, two deaths were reported, one in a Flublok recipient and one in a placebo recipient. Both deaths occurred more than 28 days following vaccination and neither was considered vaccine-related. SAEs were reported by 32 Flublok recipients and 35 placebo recipients. One SAE in a Flublok recipient was assessed as possibly related to the vaccine: pleuropericarditis with effusions requiring hospitalization and drainage. No specific cause was identified. The patient recovered.

Among adults 50 through 64 years of age (Studies 2 and 4 pooled), through up to 6 months or 30 days, post- vaccination, respectively, there were no deaths; SAEs were reported by 10 subjects, 6 Flublok recipients and 4 IIV3 recipients. One of the SAEs, vasovagal syncope following injection of Flublok, was considered related to administration of study vaccine. Among adults 65 years of age and older (Studies 3 and 4 pooled), through up to 6 months or 30 days post-vaccination, respectively, there were 4 deaths, 2 in Flublok recipients and 2 in IIV3 recipients. None were considered related to the study vaccines. SAEs were reported from 80 subjects, 37 Flublok recipients, 43 in IIV3 recipients. No SAEs were considered related to the study vaccines.

In Study 1 (adults 18 through 49 years of age), the most frequent unsolicited adverse events, occurring in 1%-2% of subjects, were nasopharyngitis, upper respiratory infection, headache, cough, nasal congestion, pharyngolaryngeal pain, and rhinorrhea.

Among adults 50 through 64 years of age (Studies 2 and 4 pooled), the most frequent unsolicited adverse events, occurring in 1% of subjects, were diarrhea and cough. Among adults ≥65 years of age (Studies 3 and 4 pooled), the most frequent unsolicited adverse events, occurring in 1% of subjects, were nasopharyngitis and cough.

Among adults 50 years of age and older (Study 4) for whom the incidence of rash, urticaria, swelling, non- pitting edema, or other potential hypersensitivity reactions were actively solicited for 30 days following vaccination, a total of 2.4% of Flublok recipients and 1.6% of IIV3 recipients reported such events over the 30 day follow-up period. A total of 1.9% and 0.9% of Flublok and IIV3 recipients, respectively, reported these events in the 7 days following vaccination. Of these solicited events, rash was most frequently reported (Flublok 1.3%, IIV3 0.8%) over the 30 day follow-up period.

Flublok Quadrivalent

Safety data were collected from 4328 adults 50 years of age and older (Study 6), 998 adults 18 through 49 years of age (Study 7), 658 adults 18 through 49 years of age (Study 8) and from 641 children and adolescents 9 through 17 years of age (Study 8) who were administered Flublok Quadrivalent.

SAEs were collected for 6 months post-vaccination via clinic visit or remote contact.

Study 6 (NCT02285998) enrolled subjects 50 years of age and older, randomized to receive Flublok Quadrivalent or Comparator (Fluarix Quadrivalent, manufactured by GlaxoSmithKline) as an active control [see Clinical Studies (14.1)]. The safety analysis population included 4328 Flublok Quadrivalent recipients and 4344 Comparator vaccine recipients. The mean age of participants was 62.7 years. Overall, 58% of subjects were female, 80% white/Caucasian, 18% black/African American, 0.9% American Indian/Alaskan Native, 0.4% Asian, 0.2% Native Hawaiian/Pacific Islander, 0.7% other racial groups, and 5% of Hispanic/Latino ethnicity.

Among adults 50 years of age and older (Study 6), there were no SAEs considered related to study vaccine.

Study 7 (NCT02290509) enrolled subjects 18 through 49 years of age randomized to receive Flublok Quadrivalent or a Comparator inactivated influenza vaccine (Fluarix® Quadrivalent, manufactured by GlaxoSmithKline). The safety analysis population included 998 recipients of Flublok Quadrivalent and 332 Comparator vaccine recipients. The mean age of participants was 33.5 years. Overall, 65% of subjects were female, 59% white/Caucasian, 37% black/African American, 1.0% Native Hawaiian/Pacific Islander, 0.8% American Indian/Alaskan Native, 0.5% Asian, 1.4% other racial groups, and 16% of Hispanic/Latino ethnicity.

Among adults 18 through 49 years of age (Study 7), through 6 months post-vaccination, there were no SAEs considered related to study vaccine.

Study 8 (NCT05513053) enrolled total of 1308 participants, 648 children and adolescents 9 through 17 years of age and 660 adults 18 through 49 years of age who were planned to receive Flublok Quadrivalent. The safety population included 641 participants 9 through 17 years of age and 658 participants 18 through 49 years of age. Among the 1299 participants in the safety population, the mean ages of participants in the 9 through 17 years and 18 through 49 years age groups were 13.0 years and 34.3 years, respectively. Overall, 54.0% of participants in the safety population were female, 76.7% White, 19.6% Black or African American, 0.5% American Indian or Alaskan Native, 0.5% Asian, 0.3% Native Hawaiian or Other Pacific Islander, and 11.4% of Hispanic/Latino ethnicity.

Solicited local and systemic adverse reactions reported within 7 days after vaccination were self-reported in electronic diaries or were reported by an investigator, and are presented in Table 4.

Table 4: Frequency of Solicited Local Injection Site Adverse Reactions and Systemic Adverse Reactions within 7 Days of Administration of Flublok Quadrivalent in Children and Adolescents 9 through 17 years of age and in Adults 18 through 49 years of age (Study 8) [Study 8 is registered as NCT05513053 under the National Clinical Trials registry.]
 | 9–17 years (N [N = the subset of randomized participants who received at least 1 dose of the study vaccine and had plausible non-missing data for the pre-specified reactions.] = 608-618) |  | 18–49 years (N = 633-635)
 | Any | Grade 3 [Grade 3 pain (≥ 12 years): Defined as significant; intensive therapeutic intervention; prevents daily activity Grade 3 pain (9 through 11 years): Incapacitating, unable to perform usual activities; significant; prevents daily activity Grade 3 erythema, swelling, induration and bruising (≥ 12 years): ≥ 100 mm Grade 3 erythema, swelling, induration and bruising (9 to 11 years): ≥ 50 mm Grade 3 myalgia, headache, malaise and chills: Defined as significant; intensive therapeutic intervention; prevents daily activity Grade 3 fever: ≥ 101.2℉ (≥ 39.0℃)] | Any | Grade 3
Local
Pain | 34.4 | 0.8 | 40.2 | 0.3
Erythema | 4.5 | 1.1 | 2.7 | 0.5
Swelling | 3.7 | 1.5 | 2.7 | 0.5
Induration | 3.1 | 0.8 | 3.3 | 0.8
Bruising | 2.4 | 0.5 | 1.1 | 0.5
Systemic
Myalgia | 19.3 | 1.5 | 20.3 | 0.9
Headache | 18.5 | 2.6 | 23.0 | 1.3
Malaise | 16.1 | 2.6 | 16.5 | 1.6
Chills | 7.3 | 0.7 | 6.3 | 0.6
Fever | 2.8 | 1.0 | 1.7 | 0.5

Unsolicited adverse events were collected through 28 days following vaccination. Unsolicited adverse events were assessed as related to the vaccine in 4.7% and 3.8% of participants in the 9 through17 years and 18 through 49 years age groups, respectively. Most unsolicited adverse events assessed as related were categorized as general disorders and administration site conditions (including one case of urticaria that began one day post vaccination), occurring in 1.7% and 1.1% of participants 9 through 17 years and 18 through 49 years of age, respectively, or as respiratory disorders (asthma, cough, nasal congestion, oropharyngeal pain, productive cough, or rhinorrhea), occurring in 1.7% and 1.5% of participants 9 through 17 years and 18 through 49 years of age, respectively. Other related events occurred in <1% of participants in either age group. No adverse reactions were considered serious.

SAEs were collected through 6 months following vaccination and were reported by 0.5% and 1.1% of participants 9 through 17 years and 18 through 49 years of age, respectively. No SAEs were considered related to the vaccine.

No deaths were reported during the study in either age group.

6.2 Postmarketing Experience

The following events have been spontaneously reported during post approval use of Flublok or Flublok Quadrivalent. They are described because of the temporal relationship, the biologic plausibility for a causal relationship to Flublok or Flublok Quadrivalent, and their potential seriousness. Because these events are reported voluntarily from a population of uncertain size, it is not always possible to reliably estimate their frequency or establish a causal relationship to vaccine exposure.

Immune system disorders: anaphylaxis, allergic reactions, and other forms of hypersensitivity (including urticaria).

Nervous system disorders: facial palsy (Bell's palsy), Guillain-Barré syndrome, syncope.

8 USE IN SPECIFIC POPULATIONS

8.1 Pregnancy

Pregnancy Exposure

There is a pregnancy exposure registry that monitors pregnancy outcomes in women exposed to Flublok.

Healthcare providers are encouraged to enroll women who receive Flublok during pregnancy in Sanofi Pasteur Inc.'s vaccination pregnancy registry by calling 1-800-822-2463 or online by completing data collection form on https://www.sanofipasteurpregnancyregistry.com.

Risk Summary

All pregnancies have a risk of birth defect, loss, or other adverse outcomes. In the U.S. general population, the estimated background rates of major birth defects and miscarriage in clinically recognized pregnancies are 2% to 4% and 15% to 20%, respectively.

Available data from a post-licensure observational, retrospective safety surveillance study showed no evidence of a vaccine-associated increase in the risk of major birth defects and miscarriages when Flublok Quadrivalent is administered during pregnancy (see Data). Data for Flublok Quadrivalent are relevant to Flublok because both vaccines are manufactured using the same process and have overlapping compositions.

A developmental study of Flublok has been performed in rats administered 0.5 mL (divided, a single human dose is 0.5 mL) of Flublok prior to mating and during gestation. This study revealed no evidence of harm to the fetus due to Flublok (see Data).

Clinical Considerations

Disease-associated Maternal and/or Embryo/Fetal Risk

Pregnant women are at increased risk of complications associated with influenza infection compared to non-pregnant women. Pregnant women with influenza may be at increased risk for adverse pregnancy outcomes, including preterm labor and delivery.

Data

Human Data

A post-licensure observational, retrospective safety surveillance study (NCT04460781) included 14,981 pregnant individuals, including those with chronic conditions, who were exposed to Flublok Quadrivalent during the 28 days prior to conception (date of conception defined as the date of the last menstrual period (Day 0) plus 14 days) or during pregnancy. The study was conducted during Northern Hemisphere influenza seasons 2018-2019 and 2019-2020. Pre-specified outcomes included spontaneous abortion and congenital/fetal anomalies. Data were not collected on ectopic pregnancy or elective terminations.

Among 14,981 recipients of Flublok Quadrivalent with known pregnancy outcomes, 750 pregnant individuals received the vaccine during the 28 days prior to conception, 5,092 during the first trimester, 4,851 during the second trimester, and 4,288 during the third trimester. Among 5,842 individuals exposed to Flublok Quadrivalent during the 28 days prior to conception or the first trimester, miscarriage was reported in 464 (3.1%). Among individuals exposed to Flublok Quadrivalent at any time during pregnancy, 1113 pregnancies (7.7%) had infants with major birth defects (56, 360, 381, and 316 among individuals exposed during the 28 days prior to conception, first trimester, second trimester and the third trimester, respectively). The consistency in rate of major birth defects, irrespective of timing of exposure to Flublok Quadrivalent (7.1% [416/5842] among individuals exposed during the 28 days prior to conception and during the first trimester, the period when the risk of major birth defects is highest, and 7.6% [697/9139] among individuals exposed during the second and third trimester) and the lack of pattern of major birth defects is reassuring.

Animal Data

In a developmental toxicity study, female rats were administered Flublok by intramuscular injection twice prior to mating (35 days and 14 days prior to mating) and on gestation Day 6. The total dose was 0.5 mL (divided) on each occasion (a human dose is 0.5 mL). No vaccine-related fetal malformations or variations and no adverse effects on pre-weaning development or female fertility were observed in the study.

8.2 Lactation

Risk Summary

It is not known whether Flublok is excreted in human milk. Data are not available to assess the effects of Flublok on the breastfed infant or on milk production/excretion.

The developmental and health benefits of breastfeeding should be considered along with the mother's clinical need for Flublok and any potential adverse effects on the breastfed child from Flublok or from the underlying maternal condition. For preventive vaccines, the underlying condition is susceptibility to disease prevented by the vaccine.

8.4 Pediatric Use

Data from two randomized controlled trials, one in children 6 through 35 months and another in children 3 through 8 years of age, showed diminished hemagglutination inhibition (HI) antibody responses to Flublok or Flublok Quadrivalent, respectively, as compared to a U.S.-licensed influenza vaccine, strongly suggesting that Flublok and Flublok Quadrivalent would not be effective in children younger than 9 years of age.

8.5 Geriatric Use

Data from an efficacy study (Study 6), which included 1759 subjects ≥65 years and 525 subjects ≥75 years who received Flublok Quadrivalent, are insufficient to determine whether elderly subjects respond differently from younger subjects (See Clinical Studies [14]). Data for Flublok Quadrivalent are relevant to Flublok because both vaccines are manufactured using the same process and have overlapping compositions.

11 DESCRIPTION

Flublok [Influenza Vaccine] is a sterile, clear, colorless injection containing recombinant hemagglutinin (HA) proteins from three influenza viruses for intramuscular use. It contains purified HA proteins produced in a continuous insect cell line (expresSF+®) that is derived from Sf9 cells of the fall armyworm, Spodoptera frugiperda (which is related to moths, caterpillars and butterflies), and grown in serum-free medium composed of chemically-defined lipids, vitamins, amino acids, and mineral salts. Each of the three HAs is expressed in this cell line using a baculovirus vector (Autographa californica nuclear polyhedrosis virus), extracted from the cells with Triton X-100 and further purified by column chromatography. The purified HAs are then blended and filled into single-dose syringes.

Flublok is standardized according to United States Public Health Service (USPHS) requirements. For the 2025-2026 influenza season it is formulated to contain 135 mcg HA per 0.5 mL dose, with 45 mcg HA of each of the following 3 influenza virus strains: A/West Virginia/30/2022 (A/Wisconsin/67/2022 pdm09-like virus) (H1N1), A/District of Columbia/27/2023 (H3N2) and B/Austria/1359417/2021.

A single 0.5 mL dose of Flublok contains sodium chloride (4.4 mg), monobasic sodium phosphate (0.2 mg), dibasic sodium phosphate (0.5 mg), and polysorbate 20 (Tween®20) (27.5 mcg). Each 0.5 mL dose of Flublok may also contain residual amounts of baculovirus and Spodoptera frugiperda cell proteins (≤ 14.3 mcg), baculovirus and cellular DNA (≤ 10 ng), and Triton X-100 (≤ 100 mcg).

Flublok contains no egg proteins, antibiotics, or preservatives. The single-dose, prefilled syringes contain no natural rubber latex.

12 CLINICAL PHARMACOLOGY

12.1 Mechanism of Action

Flublok contains recombinant HA proteins of the three strains of influenza virus specified by health authorities for inclusion in the annual seasonal vaccine. These proteins function as antigens which induce a humoral immune response, measured by hemagglutination inhibition (HI) antibody.

Antibodies against one influenza virus type or subtype confer limited or no protection against another. Furthermore, antibodies to one antigenic variant of influenza virus might not protect against a new antigenic variant of the same type or subtype. Frequent development of antigenic variants through antigenic drift is the virologic basis for seasonal epidemics and the reason for the usual replacement of one or more influenza virus strains in each year's influenza vaccine.

13 NONCLINICAL TOXICOLOGY

13.1 Carcinogenesis, Mutagenesis, Impairment of Fertility

Flublok has not been evaluated for carcinogenic or mutagenic potential, or for impairment of male fertility in animals.

14 CLINICAL STUDIES

14.1 Efficacy in Adults 18 through 49 Years of Age

The efficacy of Flublok in protecting against culture-confirmed influenza illness was evaluated in a randomized, observer-blind, placebo-controlled multicenter trial conducted in the U.S. during the 2007-2008 influenza season in adults 18 through 49 years of age (Study 1).

Study 1 enrolled and vaccinated 4648 healthy adults (mean age 32.5 years) randomized in a 1:1 ratio to receive a single dose of Flublok (n=2344) or saline placebo (n=2304). Among enrolled subjects, 59% were female, 67% were white, 19% African-American, 2% Asian, < 1% other races, and 11% of Latino/Hispanic ethnicity. Culture-confirmed influenza was assessed by active and passive surveillance for influenza-like illness (ILI) beginning 2 weeks post-vaccination until the end of the influenza season, approximately 7 months post- vaccination. ILI was defined as having at least 2 of 3 symptoms (no specified duration) in the following categories: 1) fever ≥ 100ºF; 2) respiratory symptoms (cough, sore throat, or runny nose/stuffy nose); or 3) systemic symptoms (myalgias, arthralgias, headache, chills/sweats, or tiredness/malaise). For subjects with an episode of ILI, nasal and throat swab samples were collected for viral culture.

The primary efficacy endpoint of Study 1 was Centers for Disease Control-defined influenza-like illness (CDC-ILI) with a positive culture for an influenza virus strain antigenically resembling a strain represented in Flublok. CDC-ILI is defined as fever of ≥100°F oral accompanied by cough, sore throat, or both on the same day or on consecutive days. Attack rates and vaccine efficacy (VE), defined as the reduction in the influenza rate for Flublok relative to placebo, were calculated for the total vaccinated cohort (n=4648).

The pre-defined success criterion for the primary efficacy analysis was that the lower bound of the 95% confidence interval (CI) of VE should be at least 40%. Vaccine efficacy against antigenically matched culture-confirmed CDC-ILI could not be determined reliably because 96% of the influenza isolates obtained from subjects in Study 1 were not antigenically matched to the strains represented in the vaccine. An exploratory analysis of VE of Flublok against all strains, regardless of antigenic match, isolated from any subject with an ILI, not necessarily meeting CDC- ILI criteria, demonstrated an efficacy estimate of 44.8% (95% CI 24.4, 60.0). See Table 5 for a presentation of VE by case definition and antigenic similarity.

Table 5: Vaccine Efficacy Against Culture-Confirmed Influenza in Healthy Adults 18 through 49 Years of Age, Study 1 [In Study 1 (NCT00539981) vaccine efficacy analyses were conducted on the Total Vaccinated Cohort (all randomized subjects who received study vaccine according to the treatment actually received and who provided data). Vaccine efficacy (VE) = 1 minus the ratio of Flublok/placebo infection rates.]
Case definition | Flublok (N=2344) |  | Saline Placebo (N=2304) |  | Flublok Vaccine Efficacy [Determined under the assumption of Poisson event rates, according to Breslow and Day, 1987.] , % | 95% Confidence Interval
 | Cases, n | Rate, % | Cases, n | Rate, % | Flublok Vaccine Efficacy [Determined under the assumption of Poisson event rates, according to Breslow and Day, 1987.] , % | 95% Confidence Interval
Positive culture with a strain represented in the vaccine
CDC-ILI, all matched strains [Meets CDC influenza-like illness (CDC-ILI) defined as fever of ≥100°F oral accompanied by cough and/or sore throat, on the same day or on consecutive days.] , [Primary endpoint of trial.] | 1 | 0.04 | 4 | 0.2 | 75.4 | (-148.0, 99.5)
Any ILI, all matched strains [All culture-confirmed cases are considered, regardless of whether they qualified as CDC-ILI.] , [Secondary endpoint of trial.] | 2 | 0.1 | 6 | 0.3 | 67.2 | (-83.2, 96.8)
Positive culture with any strain, regardless of match to the vaccine
CDC-ILI, all strains, [Exploratory (prespecified) endpoint of trial.] | 44 | 1.9 | 78 | 3.4 | 44.6 | (18.8, 62.6)
Sub-Type A | 26 | 1.1 | 56 | 2.4 | 54.4 | (26.1, 72.5)
Type B | 18 | 0.8 | 23 | 1.0 | 23.1 | (-49.0, 60.9)
Any ILI, all strains | 64 | 2.7 | 114 | 4.9 | 44.8 | (24.4, 60.0)
Sub-Type A | 41 | 1.7 | 79 | 3.4 | 49.0 | (24.7, 65.9)
Type B | 23 | 1.0 | 36 | 1.6 | 37.2 | (-8.9, 64.5)

14.2 Efficacy in Adults 50 Years of Age and Older

The efficacy of Flublok Quadrivalent is relevant to Flublok because both vaccines are manufactured using the same process and have overlapping compositions (see Description [11]).

Study 6 evaluated the efficacy of Flublok Quadrivalent in a randomized, observer-blind, active-controlled, multi-center trial conducted during the 2014-2015 influenza season in adults 50 years of age and older. A total of 8963 healthy, medically stable adults (mean age 62.5 years) were randomized in a 1:1 ratio to receive a single dose of Flublok Quadrivalent (n=4474) or a U.S.-licensed quadrivalent inactivated influenza vaccine (Comparator, Fluarix Quadrivalent, manufactured by Glaxo SmithKline) (n=4489).

Among randomized subjects, 58% were female, 80% white, 18% black/African-American, 2% other races, and 5% of Hispanic/Latino ethnicity. A total of 5186 (60%) subjects were 50 through 64 years of age and 3486 (40%) were ≥65 years of age. Real-time polymerase chain reaction (rtPCR) -confirmed influenza was assessed by active and passive surveillance for influenza-like illness (ILI) beginning 2 weeks post- vaccination until the end of the influenza season, approximately 6 months post- vaccination. ILI was defined as having at least one symptom (no specified duration) in each of two categories of respiratory and systemic symptoms. Respiratory symptoms included sore throat, cough, sputum production, wheezing and difficulty breathing. Systemic symptoms included fever > 99°F (>37°C) oral, chills, fatigue, headache and myalgia. For subjects with an episode of ILI, a nasopharyngeal swab sample was collected for rtPCR testing and reflex viral culture of rtPCR-positive samples.

The primary efficacy endpoint of Study 6 was rtPCR-positive, protocol-defined ILI due to any strain of influenza. Attack rates and relative vaccine efficacy (rVE), defined as 1 – [Attack rate Flublok Quadrivalent/ Attack Rate Comparator], were calculated for the total efficacy population (n=8604) for the primary efficacy endpoint and for several alternative efficacy endpoints (Table 6). Antigenic and phylogenetic evaluations of the similarity ("matching") of clinical isolates to vaccine antigens were not performed. CDC epidemiological data for the 2014-2015 influenza season indicated that Influenza A (H3N2) viruses predominated and that most influenza A/H3N2 viruses were antigenically dissimilar while A/H1N1 and B viruses were antigenically similar to vaccine antigens.

Table 6: Relative Vaccine Efficacy (rVE) of Flublok Quadrivalent versus Comparator against Laboratory-Confirmed Influenza, Regardless of Antigenic Similarity to Vaccine Antigens, Adults 50 Years of Age and Older, Study 6 (Efficacy Population) [Study 6 is registered as NCT02285998.] , [Efficacy Population included all randomized subjects who received study vaccine and provided any follow-up documentation for influenza-like illness beginning at least 14 days post-vaccination. Excluded subjects with protocol deviations that could adversely affect efficacy.]
 | Flublok Quadrivalent (N=4303) |  | Comparator (N=4301) |  |  | rVE % (95% CI)
 | n | Attack Rate % (n/N) | n | Attack Rate % (n/N) | RR | rVE % (95% CI)
All rtPCR-positive Influenza [Primary Analysis. All cases of rtPCR-confirmed influenza are included. Antigenic characterization and genetic sequencing to determine similarity of isolates to vaccine antigens were not performed. CDC surveillance data indicated that the majority of influenza A/H3N2 wild type viruses were antigenically distinct whereas influenza A/H1N1 and type B viruses were antigenically similar to vaccine antigens during the 2014-2015 season. Study 6 met the pre-specified success criterion for the primary endpoint (lower limit of the 2-sided 95% CI of vaccine efficacy for Flublok Quadrivalent relative to Comparator should be not less than - 20%).] | 96 | 2.2 | 138 | 3.2 | 0.70 | 30 (10, 47)
All rtPCR-positive Influenza A [Post hoc analyses. All cases of influenza A were A/H3N2. Cases of influenza B were not distinguished by lineage.] | 73 | 1.7 | 114 | 2.7 | 0.64 | 36 (14, 53)
All rtPCR-positive Influenza B | 23 | 0.5 | 24 | 0.6 | 0.96 | 4 (-72, 46)
All Culture-confirmed Protocol- defined ILI, [Culture of rtPCR-positive samples was performed in MDCK cells.] | 58 | 1.3 | 101 | 2.3 | 0.57 | 43 (21, 59)
Abbreviations: rtPCR=reverse transcriptase polymerase chain reaction; Comparator=U.S.-licensed quadrivalent inactivated influenza vaccine, Fluarix Quadrivalent, manufactured by GlaxoSmithKline; n=number of influenza cases; N=number of subjects in treatment group; RR=relative risk (Attack Rate Flublok/Attack Rate IIV4); rVE = [(1-RR) × 100].

14.3 Immunogenicity in Children and Adolescents 9 through 17 Years of Age

Effectiveness in children and adolescents 9 years through 17 years of age is based on a comparison of immune responses in this age group to adults 18 years through 49 years of age.

Study 8 (NCT05513053), a phase 3 non-randomized, open label, uncontrolled, multi-center study, enrolled a total of 1308 participants 9 through 49 years of age. (see Adverse Reactions [6.1]).

The primary objective was to demonstrate that vaccination with Flublok Quadrivalent induced an immune response (geometric mean titers [GMTs] and seroconversion [SCR] rates, as assessed by HI in children and adolescents 9 through 17 years of age that was non-inferior to responses induced by Flublok Quadrivalent in adults 18 through 49 years of age for the 4 virus strains at Day 29 post-vaccination.

The non-inferiority of HI immune responses induced by Flublok Quadrivalent in children and adolescents 9 through 17 years of age relative to adults 18 through 49 years of age was demonstrated for all four strains based on pre-specified criteria [lower limit of the 2-sided 95% CIs of the ratios of GMTs between age groups (9 through 17 years/18 through 49 years) > 0.667; lower limit of the 2-sided 95% CI of the difference in seroconversion rates > -10 at Day 29 post-vaccination.] (Table 7 and 8).

Table 7: Post vaccination HI GMTs and GMT Ratios in Participants 9 through 17 years vs 18 through 49 years of age, Study 8 (Per-Protocol Analysis Set) [Study 8 is registered as NCT05513053 in the National Clinical Trials registry.] , [The per-protocol analysis set is the subset of the full analysis set population with no major and/or critical deviations affecting immunogenicity.]
Antigen/strain | GMT (95% CI) 9–17 years (N=609) | GMT (95% CI) 18–49 years (N=606) | GMT Ratio 9–17 years / 18–49 years (95% CI) [Non-inferiority criteria for GMT ratio: lower limit of the 2-sided 95% CI for the GMT ratio 9–17 years / 18–49 years must be >0.667 for all 4 antigen strains.]
A/H1N1 | 1946 (1795, 2109) | 982 (881, 1094) | 1.98 (1.73; 2.27)
A/H3N2 | 1975 (1771, 2202) | 604 (531, 687) | 3.27 (2.76; 3.87)
B/Victoria | 405 (362, 452) | 258 (233, 285) | 1.57 (1.35; 1.82)
B/Yamagata | 1941 (1779, 2118) | 1593 (1477, 1717) | 1.22 (1.09; 1.37)
Abbreviations: CI, confidence interval; GMT, geometric mean titer.

Table 8: Seroconversion Rates and Seroconversion Rate Differences Postvaccination in Participants 9 through 17 years vs 18 through 49 years of age, Study 8 (Per-Protocol Analysis Set) [Study 8 is registered as NCT05513053 in the National Clinical Trials registry.] , [The per-protocol analysis set is a subset of the full analysis set population (participants who received one dose of study vaccine and provided a post-vaccination blood sample) with no major and/or critical deviations affecting immunogenicity.]
Antigen/strain | SCR %, (95% CI) 9–17 years (N=609) | SCR %, (95% CI) 18–49 years (N=606) | SCR Difference (%) 9–17 years minus 18–49 years (95% CI) [Non-inferiority criteria for SCR difference: lower limit of the 2-sided 95% CI for the SCR difference 9–17 years minus 18–49 years must be > -10% for all 4 antigen strains.]
A/H1N1 | 78.3 (74.8 ; 81.5) | 76.4 (72.8 ; 79.7) | 1.92 (-2.78; 6.62)
A/H3N2 | 86.5 (83.6 ; 89.1) | 87.1 (84.2 ; 89.7) | -0.59 (-4.41; 3.23)
B/Victoria | 76.8 (73.3 ; 80.1) | 73.6 (69.8 ; 77.0) | 3.29 (-1.57; 8.14)
B/Yamagata | 77.2 (73.6 ; 80.5) | 62.9 (58.9 ; 66.7) | 14.3 (9.17; 19.3)
Abbreviations: CI, confidence interval; SCR, seroconversion rates
Seroconversion is defined as either a pre-dose titer < 1:10 at Day 1 and a post-dose titer ≥ 1:40 at Day 29 or a pre-dose titer ≥ 1:10 at Day 29 and >= 4-fold increase in post-vaccination titer.

16 HOW SUPPLIED/STORAGE AND HANDLING

16.1 How Supplied

Flublok is supplied as a single-dose, 0.5 mL prefilled syringe in a 10 syringe carton.

Presentation | Carton NDC Number | Components and NDC Number
Single-Dose Prefilled Syringe | 49281-725-10 | Ten 0.5 mL single-dose prefilled syringes [49281-725-88]

16.2 Storage and Handling

- Store refrigerated between 2° and 8°C (36° and 46°F).
- Do not freeze. Discard if product has been frozen.
- Protect syringes from light.
- Do not use after expiration date shown on the label.

17 PATIENT COUNSELING INFORMATION

Inform the vaccine recipient of the potential benefits and risks of vaccination with Flublok. Inform the vaccine recipient that:

- Flublok contains non-infectious proteins that cannot cause influenza.
- Flublok stimulates the immune system to produce antibodies that help protect against influenza viruses contained in the vaccine but does not prevent other respiratory infections.

Instruct the vaccine recipient to report any adverse events to their healthcare provider and/or to the Vaccine Adverse Event Reporting System (VAERS).

Provide the vaccine recipient with the Vaccine Information Statements which are required by the National Childhood Vaccine Injury Act of 1986 to be given prior to vaccination. These materials are available free of charge at the Centers for Disease Control (CDC) website (www.cdc.gov/vaccines).

Encourage women who receive Flublok while pregnant to notify Sanofi Pasteur Inc. sanofipasteurpregnancyregistry.com or by calling 1-800-822-2463 (1-800-VACCINE).

Instruct the vaccine recipient that annual vaccination to prevent influenza is recommended.

Manufactured by Protein Sciences Corporation (Pearl River, NY) U.S. license No. 1795.

Distributed by Sanofi Pasteur Inc.

Flublok is a registered trademark of Protein Sciences Corporation.

This product's labeling may have been updated. For the most recent prescribing information, please visit https://dailymed.nlm.nih.gov/dailymed/.

© 2024, Sanofi Pasteur Inc. – All rights reserved

PRINCIPAL DISPLAY PANEL - 0.5 mL Syringe Carton

NDC 49281-725-10

2025-2026
Formula

Influenza Vaccine
Flublok®

Rx only

For Intramuscular Use
For 9 Years of Age and Older
10 single-dose prefilled syringes 0.5 mL each

sanofi

PRINCIPAL DISPLAY PANEL - 0.5 mL Syringe Vial

934388

Lot XXXXXXX
EXP XXXX/XX

NDC 49281-725-88

Influenza Vaccine
Flublok®
2025-2026 Formula
Rx only

No Preservative
For Intramuscular Use
0.5 mL Single-Dose
Mfd by: Protein Sciences Corp.